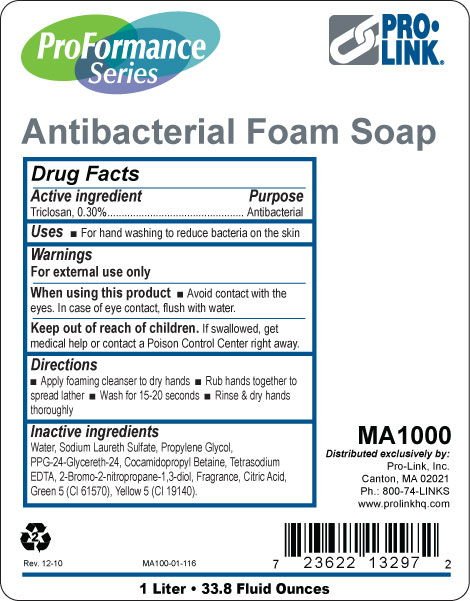 DRUG LABEL: ProFormance Series Antibacterial 
NDC: 66908-053 | Form: LIQUID
Manufacturer: Pro-Link, Inc.
Category: otc | Type: HUMAN OTC DRUG LABEL
Date: 20110103

ACTIVE INGREDIENTS: TRICLOSAN 0.30 mL/100 mL
INACTIVE INGREDIENTS: WATER; SODIUM LAURETH SULFATE; PROPYLENE GLYCOL; COCAMIDOPROPYL BETAINE; EDETATE SODIUM; ANHYDROUS CITRIC ACID; D&C GREEN NO. 5; FD&C YELLOW NO. 5

Drug Facts

Active ingredient

Triclosan, 0.30%

Purpose

Antibacterial

Uses

For hand washing to reduce bacteria on the skin

Warnings

For external use only

When using this product avoid contact with the eyes.

In case of eye contact, flush with water.

Keep out of reach of children.

If swallowed, get medical help or contact a Poison Control Center right away.

DOSAGE AND ADMINISTRATION

Enter section text here

Directions

Apply foaming cleanser to dry hands

Rub hands together to spread lather

Wash for 15-20 seconds

Rinse and dry hands thoroughly

Inactive ingredients

Water, Sodium Laureth Sulfate, Propylene Glycol, PPG-24-Glycereth-24, Cocamidopropyl Betaine, Tetrasodium EDTA, 2-Bromo-2-nitropropane-1,3-diol, Fragrance, Citric Acid, Green 5 (CI 61570), Yellow 5 (CI 19140).

PACKAGE LABEL

ProFormance Series

Antibacterial Foam Soap

Pro-Link

MA1000

Distributed exclusively by Pro-Link, Inc.

1 Liter

33.8 Fluid Ounces